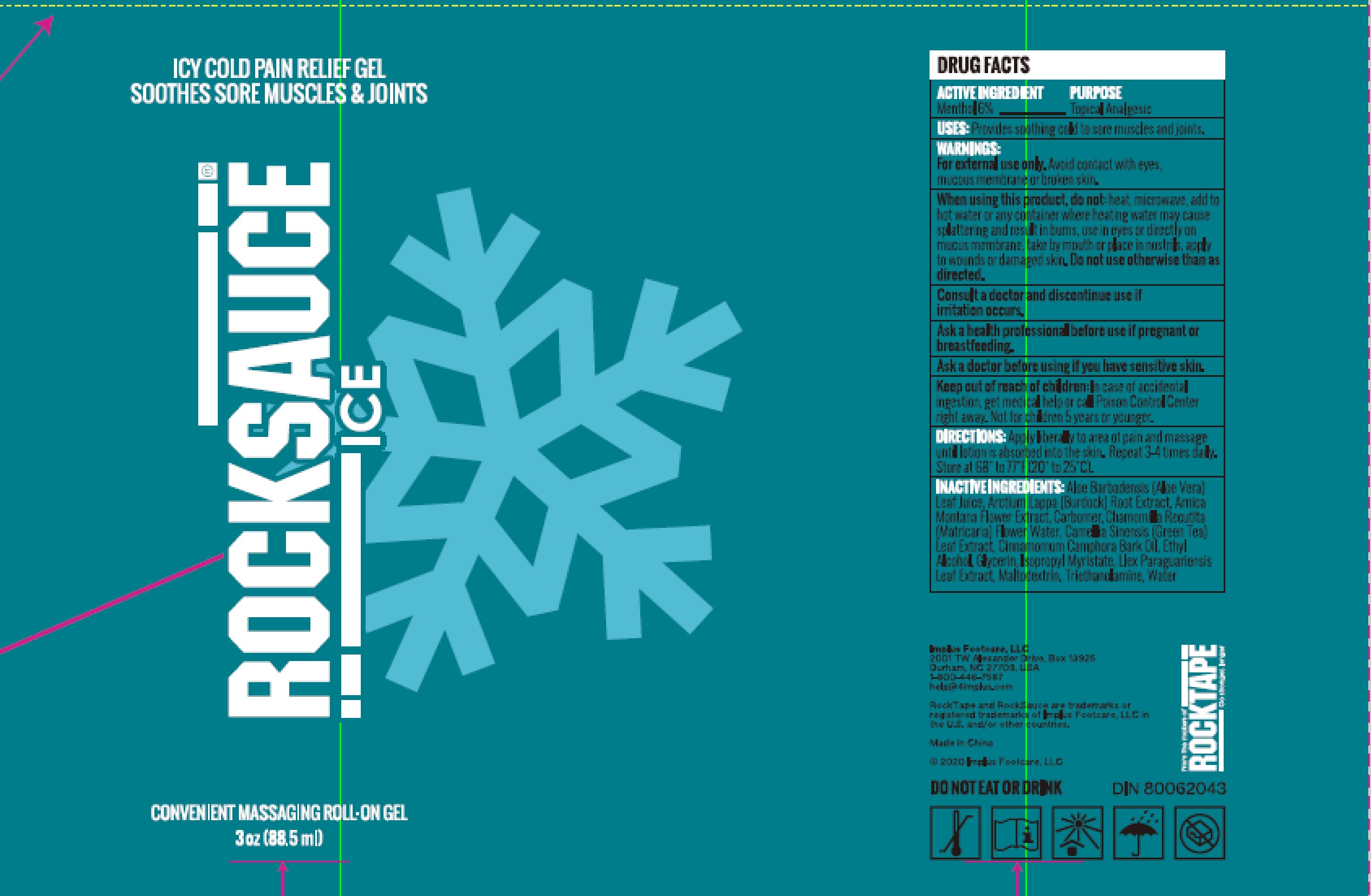 DRUG LABEL: RockSauce ICY COLD PAIN RELIEF
NDC: 81683-003 | Form: GEL
Manufacturer: Implus Footcare, LLC
Category: otc | Type: HUMAN OTC DRUG LABEL
Date: 20250407

ACTIVE INGREDIENTS: MENTHOL 8.3 g/88.5 mL
INACTIVE INGREDIENTS: ILEX PARAGUARIENSIS LEAF; ARCTIUM LAPPA ROOT; CHAMOMILE FLOWER OIL; GREEN TEA LEAF; CARBOMER 940; ALOE VERA LEAF; CAMPHOR OIL; ISOPROPYL MYRISTATE; MALTODEXTRIN; WATER; GLYCERIN; TROLAMINE; ARNICA MONTANA FLOWER; ALCOHOL

81683-003

ACTIVE INGREDIENT

Menthol6%

PURPOSE

Topical Analgesic

USES:

Provides soothing cold to sore muscles and joints.

WARNINGS:

For external use only. Avoid contact with eyes, mucous membrane or broken skin.

When using this product, do not:

heat, microwave, add to hot water or any container where heating water may cause splattering and result in burns, use in eyes or directly on mucus membrane, take by mouth or place in nostrils, apply to wounds or damaged skin.

Do not use otherwise than as directed.

ASK DOCTOR

Consult a doctor and discontinue use if irritation occurs.

Ask a health professional before use if pregnant or breastfeeding.

Ask a doctor before using if you have sensitive skin.

Keep out of reach of children:

In case of accidental ingestion, get medical help or call Poison Control Center right away. Not for children 5 years or younger.

DIRECTIONS:

Apply liberally to area of pain and massage until lotion is absorbed into the skin. Repeat 3-4 times daily. Store at 68° to 77 ℉(20° to 25℃).

INACTIVE INGREDIENTS:

Aloe Barbadensis(Aloe Vera) Leaf Juice, Arctium Lappa(Burdock)Root Extract, Arnica Montana Flower Extract, Carbomer, Chamomilla Recutita (Matricaria) Flower Water, Camellia Sinensis(Green Tea) Leaf Extract, Cinnamomum Camphora Bark Oil, Ethyl Alcohol, Glycerin, Isopropyl Myristate, Ilex Paraguariensis Leaf Extract, Maltodextrin, Triethanolamine, Water